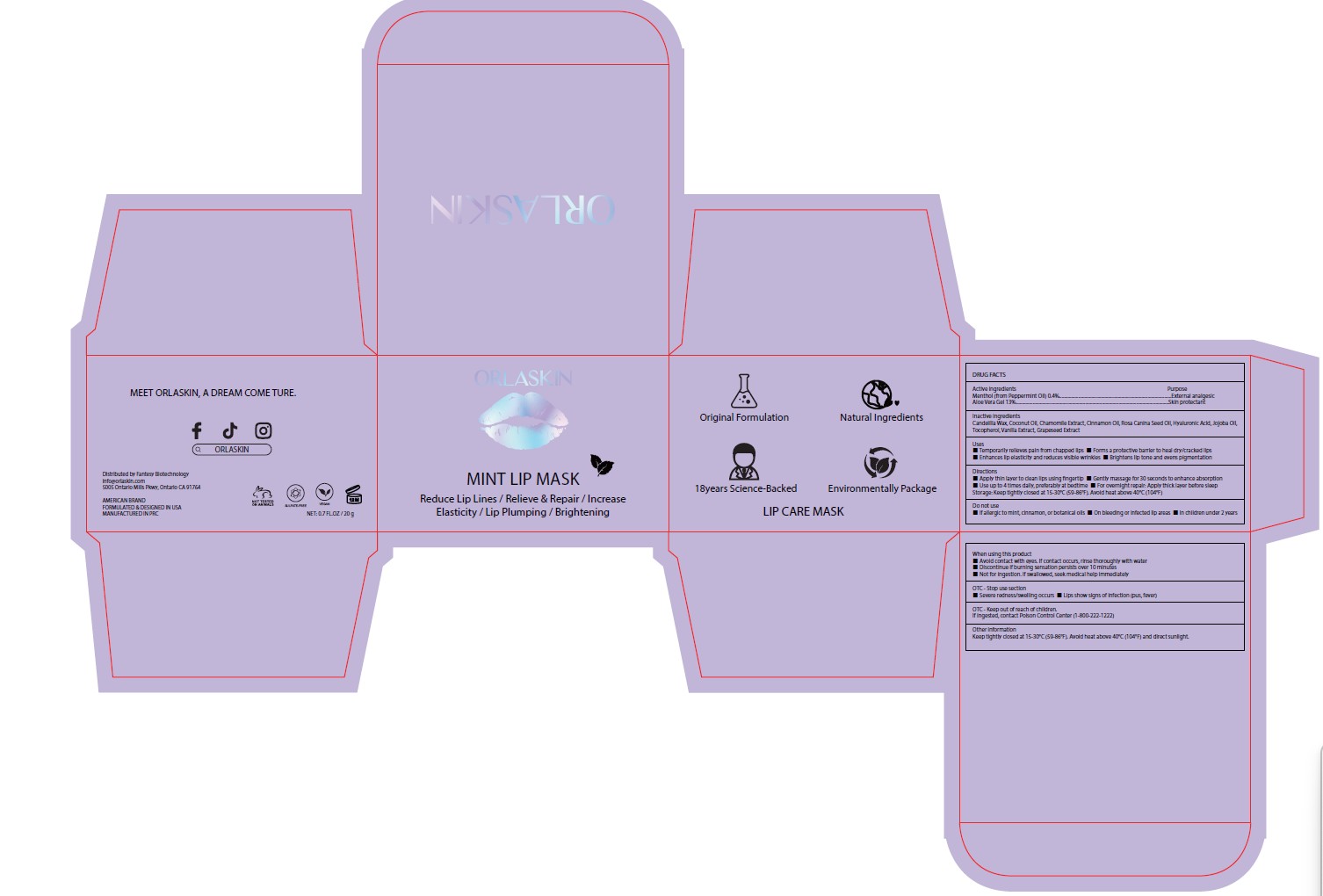 DRUG LABEL: Reduce Lip Lines
NDC: 84356-007 | Form: OINTMENT
Manufacturer: Guangzhou Yapeng Refinement Chemical Co., Ltd.
Category: otc | Type: HUMAN OTC DRUG LABEL
Date: 20250620

ACTIVE INGREDIENTS: ALOE VERA LEAF JUICE 13 g/100 g; MENTHOL 0.4 g/100 g
INACTIVE INGREDIENTS: CHAMOMILE; COCONUT OIL; HYALURONIC ACID; GRAPE SEED EXTRACT; ROSA CANINA SEED OIL; TOCOPHEROL; CANDELILLA WAX; JOJOBA OIL; CINNAMON OIL; VANILLA

ACTIVE INGEREDIENT SECTION

Menthol (from Peppermint Oil) 0.4%

Aloe Vera Gel 13%

INACTIVE INGREDIENT

Candelilla Wax, Coconut Oil, Chamomile Extract, Cinnamon Oil, ROSA CANINA SEED OIL, Hyaluronic Acid, Jojoba Oil, Tocopherol, Vanilla Extract, Grapeseed Extract

PURPOSE

Temporarily relieves pain from chapped lips,Forms a protective barrier to heal dry/cracked lips,Enhances lip elasticity and reduces visible wrinkles,Brightens lip tone and evens pigmentation

KEEP OUT OF REACH OF CHILDREN

If ingested, contact Poison Control Center

STOP USE

If allergic to mint, cinnamon, or botanical oils

On bleeding or infected lip areas

In children under 2 years

WHEN USING

Avoid contact with eyes. If contact occurs, rinse thoroughly with water
Discontinue if burning sensation persists over 10 minutes
Not for ingestion. If swallowed, seek medical help immediately

WARNINGS

If allergic to mint, cinnamon, or botanical oils,On bleeding or infected lip areas,In children under 2 years

DOSAGE AND ADMINISTRATION

Apply thin layer to clean lips using fingertip Gently massage for 30 seconds to enhance absorption Use up to 4 times daily, preferably at bedtime For overnight repair: Apply thick layer before sleep

RECENT MAJOR CHANGES

Reduce Lip Lines
Relieve & Repair
Increase Elasticity
Lip Plumping
Brightening

STORAGE AND HANDLING

Keep tightly closed at 15-30°C (59-86°F). Avoid heat above 40°C (104°F) and direct sunlight.

INDICATIONS AND USAGE

Reduce Lip Lines
Relieve & Repair
Increase Elasticity
Lip Plumping
Brightening